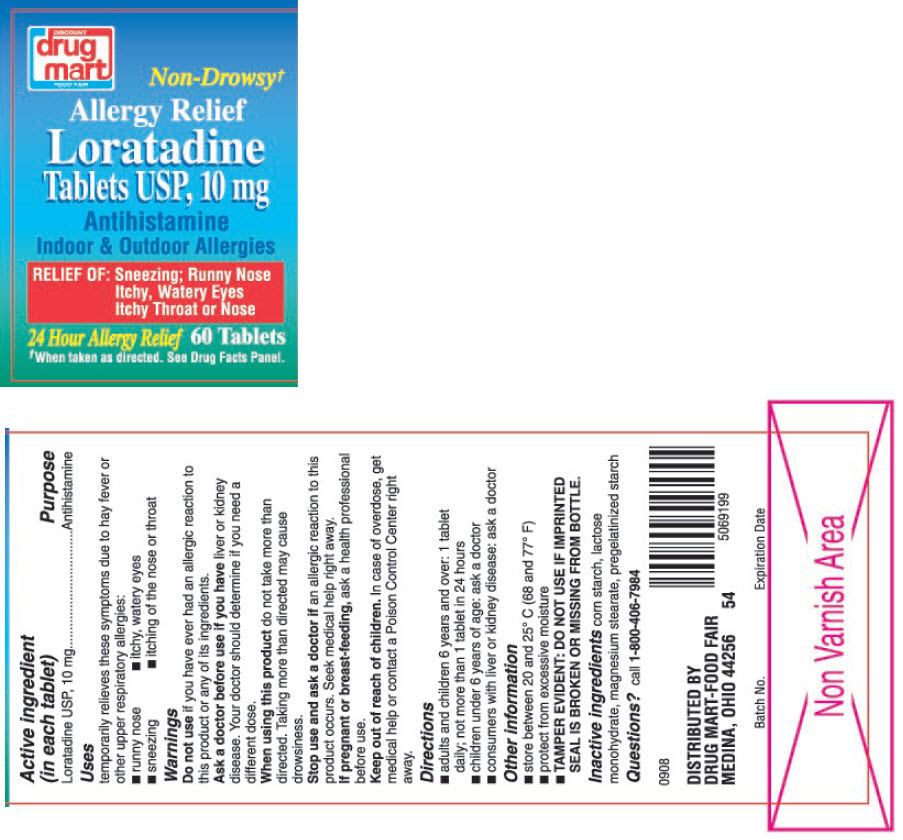 DRUG LABEL: Loratadine Allergy Relief
NDC: 53943-975 | Form: TABLET
Manufacturer: DISCOUNT DRUG MART
Category: otc | Type: HUMAN OTC DRUG LABEL
Date: 20180914

ACTIVE INGREDIENTS: LORATADINE 10 mg/1 1
INACTIVE INGREDIENTS: STARCH, CORN; LACTOSE MONOHYDRATE; MAGNESIUM STEARATE

Loratadine Allergy Relief

Active ingredient (in each tablet)

Loratadine USP, 10 mg

Purpose

Antihistamine

Uses

temporarily relieves these symptoms due to hay fever or other upper respiratory allergies:

- runny nose
- itchy, watery eyes
- sneezing
- itching of the nose or throat

Warnings

Do not use if you have ever had an allergic reaction to this product or any of its ingredients.

Ask a doctor before use if you have liver or kidney disease. Your doctor should determine if you need a different dose.

When using this product do not take more than directed. Taking more than directed may cause drowsiness.

Stop use and ask a doctor if an allergic reaction to this product occurs. Seek medical help right away.

PREGNANCY OR BREAST FEEDING

If pregnant or breast-feeding, ask a health professional before use.

Keep out of reach of children. In case of overdose, get medical help or contact a Poison Control Center right away.

Directions

- adults and children 6 years and over: 1 tablet daily; not more than 1 tablet in 24 hours
- children under 6 years of age: ask a doctor
- consumers with liver or kidney disease: ask a doctor

Other information

- store between 20 and 25° C (68 and 77° F)
- protect from excessive moisture
- TAMPER EVIDENT: DO NOT USE IF IMPRINTED SEAL IS BROKEN OR MISSING FROM BOTTLE.

Inactive ingredients

corn starch, lactose monohydrate, magnesium stearate, pregelatinized starch

Questions?

call 1-800-406-7984

DISTRIBUTED BY
DRUG MART-FOOD FAIR
MEDINA, OHIO 44256

PRINCIPAL DISPLAY PANEL - 10 mg Tablet Bottle Label

DISCOUNT
drug
mart
FOOD FAIR

Non-Drowsy†

Allergy Relief

Loratadine
Tablets USP, 10 mg

Antihistamine
Indoor & Outdoor Allergies

RELIEF OF: Sneezing; Runny Nose
Itchy, Watery Eyes
Itchy Throat or Nose

24 Hour Allergy Relief

60 Tablets

†When taken as directed. See Drug Facts Panel.